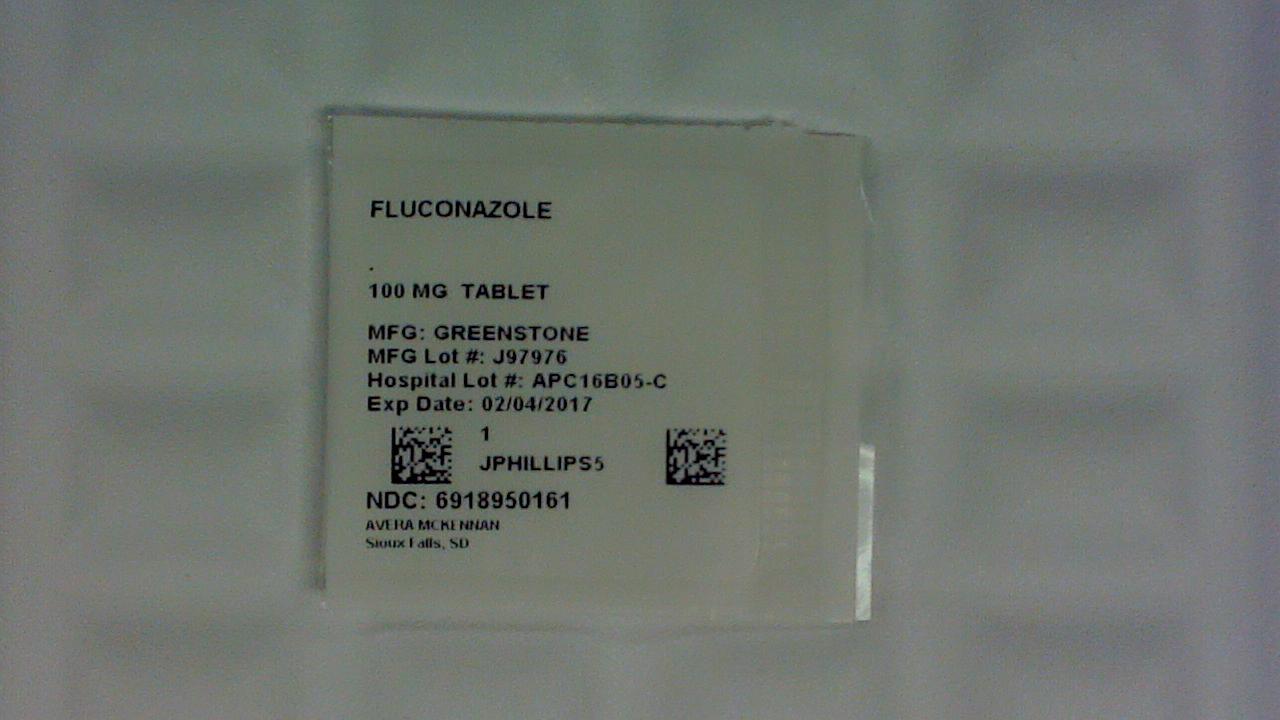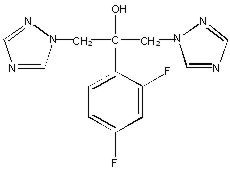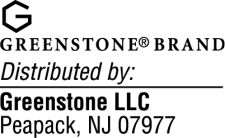 DRUG LABEL: Fluconazole
NDC: 69189-5016 | Form: TABLET
Manufacturer: Avera McKennan Hospital
Category: prescription | Type: HUMAN PRESCRIPTION DRUG LABEL
Date: 20170317

ACTIVE INGREDIENTS: FLUCONAZOLE 100 mg/1 1
INACTIVE INGREDIENTS: CELLULOSE, MICROCRYSTALLINE; ANHYDROUS DIBASIC CALCIUM PHOSPHATE; POVIDONES; CROSCARMELLOSE SODIUM; FD&C RED NO. 40; ALUMINUM OXIDE; MAGNESIUM STEARATE

FLUCONAZOLE
Fluconazole Tablets
Fluconazole for Oral Suspension

DESCRIPTION

Fluconazole, the first of a new subclass of synthetic triazole antifungal agents, is available as tablets for oral administration and as a powder for oral suspension.

Fluconazole is designated chemically as 2,4-difluoro-α,α^1-bis(1H-1,2,4-triazol-1-ylmethyl) benzyl alcohol with an empirical formula of C13H12F2N6O and molecular weight of 306.3. The structural formula is:

Fluconazole is a white crystalline solid which is slightly soluble in water and saline.

Fluconazole Tablets contain 50, 100, 150, or 200 mg of fluconazole and the following inactive ingredients: microcrystalline cellulose, dibasic calcium phosphate anhydrous, povidone, croscarmellose sodium, FD&C Red No. 40 aluminum lake dye, and magnesium stearate.

Fluconazole for Oral Suspension contains 350 mg or 1400 mg of fluconazole and the following inactive ingredients: sucrose, sodium citrate dihydrate, citric acid anhydrous, sodium benzoate, titanium dioxide, colloidal silicon dioxide, xanthan gum, and natural orange flavor. After reconstitution with 24 mL of distilled water or Purified Water (USP), each mL of reconstituted suspension contains 10 mg or 40 mg of fluconazole.

CLINICAL PHARMACOLOGY

Pharmacokinetics and Metabolism

The pharmacokinetic properties of fluconazole are similar following administration by the intravenous or oral routes. In normal volunteers, the bioavailability of orally administered fluconazole is over 90% compared with intravenous administration. Bioequivalence was established between the 100 mg tablet and both suspension strengths when administered as a single 200 mg dose.

Peak plasma concentrations (Cmax) in fasted normal volunteers occur between 1 and 2 hours with a terminal plasma elimination half-life of approximately 30 hours (range: 20–50 hours) after oral administration.

In fasted normal volunteers, administration of a single oral 400 mg dose of fluconazole leads to a mean Cmax of 6.72 µg/mL (range: 4.12 to 8.08 µg/mL) and after single oral doses of 50–400 mg, fluconazole plasma concentrations and AUC (area under the plasma concentration-time curve) are dose proportional.

The Cmax and AUC data from a food-effect study involving administration of fluconazole tablets to healthy volunteers under fasting conditions and with a high-fat meal indicated that exposure to the drug is not affected by food. Therefore, fluconazole may be taken without regard to meals. (see DOSAGE AND ADMINISTRATION.)

Administration of a single oral 150 mg tablet of fluconazole to ten lactating women resulted in a mean Cmax of 2.61 µg/mL (range: 1.57 to 3.65 µg/mL).

Steady-state concentrations are reached within 5–10 days following oral doses of 50–400 mg given once daily. Administration of a loading dose (on day 1) of twice the usual daily dose results in plasma concentrations close to steady-state by the second day. The apparent volume of distribution of fluconazole approximates that of total body water. Plasma protein binding is low (11–12%). Following either single- or multiple oral doses for up to 14 days, fluconazole penetrates into all body fluids studied (see table below). In normal volunteers, saliva concentrations of fluconazole were equal to or slightly greater than plasma concentrations regardless of dose, route, or duration of dosing. In patients with bronchiectasis, sputum concentrations of fluconazole following a single 150 mg oral dose were equal to plasma concentrations at both 4 and 24 hours post dose. In patients with fungal meningitis, fluconazole concentrations in the CSF are approximately 80% of the corresponding plasma concentrations.

A single oral 150 mg dose of fluconazole administered to 27 patients penetrated into vaginal tissue, resulting in tissue:plasma ratios ranging from 0.94 to 1.14 over the first 48 hours following dosing.

A single oral 150 mg dose of fluconazole administered to 14 patients penetrated into vaginal fluid, resulting in fluid:plasma ratios ranging from 0.36 to 0.71 over the first 72 hours following dosing.

Tissue or Fluid | Ratio of Fluconazole Tissue (Fluid)/Plasma Concentration [Relative to concurrent concentrations in plasma in subjects with normal renal function.]
Cerebrospinal fluid [Independent of degree of meningeal inflammation.] | 0.5–0.9
Saliva | 1
Sputum | 1
Blister fluid | 1
Urine | 10
Normal skin | 10
Nails | 1
Blister skin | 2
Vaginal tissue | 1
Vaginal fluid | 0.4–0.7

In normal volunteers, fluconazole is cleared primarily by renal excretion, with approximately 80% of the administered dose appearing in the urine as unchanged drug. About 11% of the dose is excreted in the urine as metabolites.

The pharmacokinetics of fluconazole are markedly affected by reduction in renal function. There is an inverse relationship between the elimination half-life and creatinine clearance. The dose of fluconazole may need to be reduced in patients with impaired renal function. (See DOSAGE AND ADMINISTRATION.) A 3-hour hemodialysis session decreases plasma concentrations by approximately 50%.

In normal volunteers, fluconazole administration (doses ranging from 200 mg to 400 mg once daily for up to 14 days) was associated with small and inconsistent effects on testosterone concentrations, endogenous corticosteroid concentrations, and the ACTH-stimulated cortisol response.

Pharmacokinetics in Children

In children, the following pharmacokinetic data {Mean (%cv)} have been reported:

Age Studied | Dose (mg/kg) | Clearance (mL/min/kg) | Half-life (Hours) | Cmax (µg/mL) | Vdss (L/kg)
9 Months– 13 years | Single-Oral 2 mg/kg | 0.40 (38%) N=14 | 25.0 | 2.9 (22%) N=16 | —
9 Months– 13 years | Single-Oral 8 mg/kg | 0.51 (60%) N=15 | 19.5 | 9.8 (20%) N=15 | —
5–15 years | Multiple IV 2 mg/kg | 0.49 (40%) N=4 | 17.4 | 5.5 (25%) N=5 | 0.722 (36%) N=4
5–15 years | Multiple IV 4 mg/kg | 0.59 (64%) N=5 | 15.2 | 11.4 (44%) N=6 | 0.729 (33%) N=5
5–15 years | Multiple IV 8 mg/kg | 0.66 (31%) N=7 | 17.6 | 14.1 (22%) N=8 | 1.069 (37%) N=7

Clearance corrected for body weight was not affected by age in these studies. Mean body clearance in adults is reported to be 0.23 (17%) mL/min/kg.

In premature newborns (gestational age 26 to 29 weeks), the mean (%cv) clearance within 36 hours of birth was 0.180 (35%, N=7) mL/min/kg, which increased with time to a mean of 0.218 (31%, N=9) mL/min/kg six days later and 0.333 (56%, N=4) mL/min/kg 12 days later. Similarly, the half-life was 73.6 hours, which decreased with time to a mean of 53.2 hours six days later and 46.6 hours 12 days later.

Pharmacokinetics in Elderly

A pharmacokinetic study was conducted in 22 subjects, 65 years of age or older receiving a single 50 mg oral dose of fluconazole. Ten of these patients were concomitantly receiving diuretics. The Cmax was 1.54 mcg/mL and occurred at 1.3 hours post dose. The mean AUC was 76.4 ± 20.3 mcg∙h/mL, and the mean terminal half-life was 46.2 hours. These pharmacokinetic parameter values are higher than analogous values reported for normal young male volunteers. Coadministration of diuretics did not significantly alter AUC or Cmax. In addition, creatinine clearance (74 mL/min), the percent of drug recovered unchanged in urine (0–24 hr, 22%), and the fluconazole renal clearance estimates (0.124 mL/min/kg) for the elderly were generally lower than those of younger volunteers. Thus, the alteration of fluconazole disposition in the elderly appears to be related to reduced renal function characteristic of this group. A plot of each subject's terminal elimination half-life versus creatinine clearance compared with the predicted half-life – creatinine clearance curve derived from normal subjects and subjects with varying degrees of renal insufficiency indicated that 21 of 22 subjects fell within the 95% confidence limit of the predicted half-life – creatinine clearance curves. These results are consistent with the hypothesis that higher values for the pharmacokinetic parameters observed in the elderly subjects compared with normal young male volunteers are due to the decreased kidney function that is expected in the elderly.

Drug Interaction Studies

Oral contraceptives

Oral contraceptives were administered as a single dose both before and after the oral administration of fluconazole 50 mg once daily for 10 days in 10 healthy women. There was no significant difference in ethinyl estradiol or levonorgestrel AUC after the administration of 50 mg of fluconazole. The mean increase in ethinyl estradiol AUC was 6% (range: −47 to 108%) and levonorgestrel AUC increased 17% (range: −33 to 141%).

In a second study, twenty-five normal females received daily doses of both 200 mg fluconazole tablets or placebo for two, ten-day periods. The treatment cycles were one month apart with all subjects receiving fluconazole during one cycle and placebo during the other. The order of study treatment was random. Single doses of an oral contraceptive tablet containing levonorgestrel and ethinyl estradiol were administered on the final treatment day (day 10) of both cycles. Following administration of 200 mg of fluconazole, the mean percentage increase of AUC for levonorgestrel compared to placebo was 25% (range: –12 to 82%) and the mean percentage increase for ethinyl estradiol compared to placebo was 38% (range: –11 to 101%). Both of these increases were statistically significantly different from placebo.

A third study evaluated the potential interaction of once weekly dosing of fluconazole 300 mg to 21 normal females taking an oral contraceptive containing ethinyl estradiol and norethindrone. In this placebo-controlled, double-blind, randomized, two-way crossover study carried out over three cycles of oral contraceptive treatment, fluconazole dosing resulted in small increases in the mean AUCs of ethinyl estradiol and norethindrone compared to similar placebo dosing. The mean AUCs of ethinyl estradiol and norethindrone increased by 24% (95% C.I. range: 18–31%) and 13% (95% C.I. range: 8–18%), respectively, relative to placebo. Fluconazole treatment did not cause a decrease in the ethinyl estradiol AUC of any individual subject in this study compared to placebo dosing. The individual AUC values of norethindrone decreased very slightly (<5%) in 3 of the 21 subjects after fluconazole treatment.

Cimetidine

Fluconazole 100 mg was administered as a single oral dose alone and two hours after a single dose of cimetidine 400 mg to six healthy male volunteers. After the administration of cimetidine, there was a significant decrease in fluconazole AUC and Cmax. There was a mean ± SD decrease in fluconazole AUC of 13% ± 11% (range: −3.4 to −31%) and Cmax decreased 19% ± 14% (range: −5 to −40%). However, the administration of cimetidine 600 mg to 900 mg intravenously over a four-hour period (from one hour before to 3 hours after a single oral dose of fluconazole 200 mg) did not affect the bioavailability or pharmacokinetics of fluconazole in 24 healthy male volunteers.

Antacid

Administration of Maalox® (20 mL) to 14 normal male volunteers immediately prior to a single dose of fluconazole 100 mg had no effect on the absorption or elimination of fluconazole.

Hydrochlorothiazide

Concomitant oral administration of 100 mg fluconazole and 50 mg hydrochlorothiazide for 10 days in 13 normal volunteers resulted in a significant increase in fluconazole AUC and Cmax compared to fluconazole given alone. There was a mean ± SD increase in fluconazole AUC and Cmax of 45% ± 31% (range: 19 to 114%) and 43% ± 31% (range: 19 to 122%), respectively. These changes are attributed to a mean ± SD reduction in renal clearance of 30% ± 12% (range: −10 to −50%).

Rifampin

Administration of a single oral 200 mg dose of fluconazole after 15 days of rifampin administered as 600 mg daily in eight healthy male volunteers resulted in a significant decrease in fluconazole AUC and a significant increase in apparent oral clearance of fluconazole. There was a mean ± SD reduction in fluconazole AUC of 23% ± 9% (range: −13 to −42%). Apparent oral clearance of fluconazole increased 32% ± 17% (range: 16 to 72%). Fluconazole half-life decreased from 33.4 ± 4.4 hours to 26.8 ± 3.9 hours. (See PRECAUTIONS.)

Warfarin

There was a significant increase in prothrombin time response (area under the prothrombin time-time curve) following a single dose of warfarin (15 mg) administered to 13 normal male volunteers following oral fluconazole 200 mg administered daily for 14 days as compared to the administration of warfarin alone. There was a mean ± SD increase in the prothrombin time response (area under the prothrombin time-time curve) of 7% ± 4% (range: −2 to 13%). (See PRECAUTIONS.) Mean is based on data from 12 subjects as one of 13 subjects experienced a 2-fold increase in his prothrombin time response.

Phenytoin

Phenytoin AUC was determined after 4 days of phenytoin dosing (200 mg daily, orally for 3 days followed by 250 mg intravenously for one dose) both with and without the administration of fluconazole (oral fluconazole 200 mg daily for 16 days) in 10 normal male volunteers. There was a significant increase in phenytoin AUC. The mean ± SD increase in phenytoin AUC was 88% ± 68% (range: 16 to 247%). The absolute magnitude of this interaction is unknown because of the intrinsically nonlinear disposition of phenytoin. (See PRECAUTIONS.)

Cyclosporine

Cyclosporine AUC and Cmax were determined before and after the administration of fluconazole 200 mg daily for 14 days in eight renal transplant patients who had been on cyclosporine therapy for at least 6 months and on a stable cyclosporine dose for at least 6 weeks. There was a significant increase in cyclosporine AUC, Cmax, Cmin (24-hour concentration), and a significant reduction in apparent oral clearance following the administration of fluconazole. The mean ± SD increase in AUC was 92% ± 43% (range: 18 to 147%). The Cmax increased 60% ± 48% (range: −5 to 133%). The Cmin increased 157% ± 96% (range: 33 to 360%). The apparent oral clearance decreased 45% ± 15% (range: −15 to −60%). (See PRECAUTIONS.)

Zidovudine

Plasma zidovudine concentrations were determined on two occasions (before and following fluconazole 200 mg daily for 15 days) in 13 volunteers with AIDS or ARC who were on a stable zidovudine dose for at least two weeks. There was a significant increase in zidovudine AUC following the administration of fluconazole. The mean ± SD increase in AUC was 20% ± 32% (range: −27 to 104%). The metabolite, GZDV, to parent drug ratio significantly decreased after the administration of fluconazole, from 7.6 ± 3.6 to 5.7 ± 2.2.

Theophylline

The pharmacokinetics of theophylline were determined from a single intravenous dose of aminophylline (6 mg/kg) before and after the oral administration of fluconazole 200 mg daily for 14 days in 16 normal male volunteers. There were significant increases in theophylline AUC, Cmax, and half-life with a corresponding decrease in clearance. The mean ± SD theophylline AUC increased 21% ± 16% (range: −5 to 48%). The Cmax increased 13% ± 17% (range: −13 to 40%). Theophylline clearance decreased 16% ± 11% (range: −32 to 5%). The half-life of theophylline increased from 6.6 ± 1.7 hours to 7.9 ± 1.5 hours. (See PRECAUTIONS.)

Terfenadine

Six healthy volunteers received terfenadine 60 mg BID for 15 days. Fluconazole 200 mg was administered daily from days 9 through 15. Fluconazole did not affect terfenadine plasma concentrations. Terfenadine acid metabolite AUC increased 36% ± 36% (range: 7 to 102%) from day 8 to day 15 with the concomitant administration of fluconazole. There was no change in cardiac repolarization as measured by Holter QTc intervals. Another study at a 400 mg and 800 mg daily dose of fluconazole demonstrated that fluconazole taken in doses of 400 mg per day or greater significantly increases plasma levels of terfenadine when taken concomitantly. (See CONTRAINDICATIONS and PRECAUTIONS.)

Quinidine

Although not studied in vitro or in vivo, concomitant administration of fluconazole with quinidine may result in inhibition of quinidine metabolism. Use of quinidine has been associated with QT prolongation and rare occurrences of torsades de pointes. Coadministration of fluconazole and quinidine is contraindicated. (See CONTRAINDICATIONS and PRECAUTIONS.)

Oral hypoglycemics

The effects of fluconazole on the pharmacokinetics of the sulfonylurea oral hypoglycemic agents tolbutamide, glipizide, and glyburide were evaluated in three placebo-controlled studies in normal volunteers. All subjects received the sulfonylurea alone as a single dose and again as a single dose following the administration of fluconazole 100 mg daily for 7 days. In these three studies, 22/46 (47.8%) of fluconazole treated patients and 9/22 (40.1%) of placebo-treated patients experienced symptoms consistent with hypoglycemia. (See PRECAUTIONS.)

Tolbutamide

In 13 normal male volunteers, there was significant increase in tolbutamide (500 mg single dose) AUC and Cmax following the administration of fluconazole. There was a mean ± SD increase in tolbutamide AUC of 26% ± 9% (range: 12 to 39%). Tolbutamide Cmax increased 11% ± 9% (range: –6 to 27%). (See PRECAUTIONS.)

Glipizide

The AUC and Cmax of glipizide (2.5 mg single dose) were significantly increased following the administration of fluconazole in 13 normal male volunteers. There was a mean ± SD increase in AUC of 49% ± 13% (range: 27 to 73%) and an increase in Cmax of 19% ± 23% (range: −11 to 79%). (See PRECAUTIONS.)

Glyburide

The AUC and Cmax of glyburide (5 mg single dose) were significantly increased following the administration of fluconazole in 20 normal male volunteers. There was a mean ± SD increase in AUC of 44% ± 29% (range: –13 to 115%) and Cmax increased 19% ± 19% (range: −23 to 62%). Five subjects required oral glucose following the ingestion of glyburide after 7 days of fluconazole administration. (See PRECAUTIONS.)

Rifabutin

There have been published reports that an interaction exists when fluconazole is administered concomitantly with rifabutin, leading to increased serum levels of rifabutin. (See PRECAUTIONS.)

Tacrolimus

There have been published reports that an interaction exists when fluconazole is administered concomitantly with tacrolimus, leading to increased serum levels of tacrolimus. (See PRECAUTIONS.)

Cisapride

A placebo-controlled, randomized, multiple-dose study examined the potential interaction of fluconazole with cisapride. Two groups of 10 normal subjects were administered fluconazole 200 mg daily or placebo. Cisapride 20 mg four times daily was started after 7 days of fluconazole or placebo dosing. Following a single dose of fluconazole, there was a 101% increase in the cisapride AUC and a 91% increase in the cisapride Cmax. Following multiple doses of fluconazole, there was a 192% increase in the cisapride AUC and a 154% increase in the cisapride Cmax . Fluconazole significantly increased the QTc interval in subjects receiving cisapride 20 mg four times daily for 5 days. (See CONTRAINDICATIONS and PRECAUTIONS.)

Midazolam

The effect of fluconazole on the pharmacokinetics and pharmacodynamics of midazolam was examined in a randomized, cross-over study in 12 volunteers. In the study, subjects ingested placebo or 400 mg fluconazole on Day 1 followed by 200 mg daily from Day 2 to Day 6. In addition, a 7.5 mg dose of midazolam was orally ingested on the first day, 0.05 mg/kg was administered intravenously on the fourth day, and 7.5 mg orally on the sixth day. Fluconazole reduced the clearance of IV midazolam by 51%. On the first day of dosing, fluconazole increased the midazolam AUC and Cmax by 259% and 150%, respectively. On the sixth day of dosing, fluconazole increased the midazolam AUC and Cmax by 259% and 74%, respectively. The psychomotor effects of midazolam were significantly increased after oral administration of midazolam but not significantly affected following intravenous midazolam.

A second randomized, double-dummy, placebo-controlled, cross-over study in three phases was performed to determine the effect of route of administration of fluconazole on the interaction between fluconazole and midazolam. In each phase the subjects were given oral fluconazole 400 mg and intravenous saline; oral placebo and intravenous fluconazole 400 mg; and oral placebo and IV saline. An oral dose of 7.5 mg of midazolam was ingested after fluconazole/placebo. The AUC and Cmax of midazolam were significantly higher after oral than IV administration of fluconazole. Oral fluconazole increased the midazolam AUC and Cmax by 272% and 129%, respectively. IV fluconazole increased the midazolam AUC and Cmax by 244% and 79%, respectively. Both oral and IV fluconazole increased the pharmacodynamic effects of midazolam. (See PRECAUTIONS.)

Azithromycin

An open-label, randomized, three-way crossover study in 18 healthy subjects assessed the effect of a single 800 mg oral dose of fluconazole on the pharmacokinetics of a single 1200 mg oral dose of azithromycin as well as the effects of azithromycin on the pharmacokinetics of fluconazole. There was no significant pharmacokinetic interaction between fluconazole and azithromycin.

Voriconazole

Voriconazole is a substrate for both CYP2C9 and CYP3A4 isoenzymes. Concurrent administration of oral Voriconazole (400 mg Q12h for 1 day, then 200 mg Q12h for 2.5 days) and oral fluconazole (400 mg on day 1, then 200 mg Q24h for 4 days) to 6 healthy male subjects resulted in an increase in Cmax and AUCτ of voriconazole by an average of 57% (90% CI: 20%, 107%) and 79% (90% CI: 40%, 128%), respectively. In a follow-on clinical study involving 8 healthy male subjects, reduced dosing and/or frequency of voriconazole and fluconazole did not eliminate or diminish this effect. Concomitant administration of voriconazole and fluconazole at any dose is not recommended. Close monitoring for adverse events related to voriconazole is recommended if voriconazole is used sequentially after fluconazole, especially within 24 h of the last dose of fluconazole. (See PRECAUTIONS.)

Tofacitinib

Co-administration of fluconazole (400 mg on Day 1 and 200 mg once daily for 6 days [Days 2-7]) and tofacitinib (30 mg single dose on Day 5) in healthy subjects resulted in increased mean tofacitinib AUC and Cmax values of approximately 79% (90% CI: 64% – 96%) and 27% (90% CI: 12% – 44%), respectively, compared to administration of tofacitinib alone. (See PRECAUTIONS.)

Microbiology

Mechanism of Action

Fluconazole is a highly selective inhibitor of fungal cytochrome P450 dependent enzyme lanosterol 14-α-demethylase. This enzyme functions to convert lanosterol to ergosterol. The subsequent loss of normal sterols correlates with the accumulation of 14-α-methyl sterols in fungi and may be responsible for the fungistatic activity of fluconazole. Mammalian cell demethylation is much less sensitive to fluconazole inhibition.

Drug Resistance

Fluconazole resistance may arise from a modification in the quality or quantity of the target enzyme (lanosterol 14-α-demethylase), reduced access to the drug target, or some combination of these mechanisms.

Point mutations in the gene (ERG11) encoding for the target enzyme lead to an altered target with decreased affinity for azoles. Overexpression of ERG11 results in the production of high concentrations of the target enzyme, creating the need for higher intracellular drug concentrations to inhibit all of the enzyme molecules in the cell.

The second major mechanism of drug resistance involves active efflux of fluconazole out of the cell through the activation of two types of multidrug efflux transporters; the major facilitators (encoded by MDR genes) and those of the ATP-binding cassette superfamily (encoded by CDR genes). Upregulation of the MDR gene leads to fluconazole resistance, whereas, upregulation of CDR genes may lead to resistance to multiple azoles.

Resistance in Candida glabrata usually includes upregulation of CDR genes resulting in resistance to multiple azoles. For an isolate where the MIC is categorized as Intermediate (16 to 32 µg/mL), the highest fluconazole dose is recommended.

Candida krusei should be considered to be resistant to fluconazole. Resistance in C. krusei appears to be mediated by reduced sensitivity of the target enzyme to inhibition by the agent.

There have been reports of cases of superinfection with Candida species other than C. albicans, which are often inherently not susceptible to fluconazole (e.g., Candida krusei). Such cases may require alternative antifungal therapy.

Activity In Vitro and In Clinical Infections

Fluconazole has been shown to be active against most strains of the following microorganisms both in vitro and in clinical infections.

Candida albicans
Candida glabrata (Many strains are intermediately susceptible) [In a majority of the studies, fluconazole MIC90 values against C. glabrata were above the susceptible breakpoint (≥16 µg/mL). Resistance in Candida glabrata usually includes upregulation of CDR genes resulting in resistance to multiple azoles. For an isolate where the MIC is categorized as intermediate (16 to 32 µg/mL, see Table 1), the highest dose is recommended (see DOSAGE AND ADMINISTRATION). For resistant isolates, alternative therapy is recommended.]
Candida parapsilosis
Candida tropicalis
Cryptococcus neoformans

The following in vitro data are available, but their clinical significance is unknown.

Fluconazole exhibits in vitro minimum inhibitory concentrations (MIC values) of 8 µg/mL or less against most (≥90%) strains of the following microorganisms, however, the safety and effectiveness of fluconazole in treating clinical infections due to these microorganisms have not been established in adequate and well-controlled trials.

Candida dubliniensis
Candida guilliermondii
Candida kefyr
Candida lusitaniae

Candida krusei should be considered to be resistant to fluconazole. Resistance in C. krusei appears to be mediated by reduced sensitivity of the target enzyme to inhibition by the agent.

There have been reports of cases of superinfection with Candida species other than C. albicans, which are often inherently not susceptible to fluconazole (e.g., Candida krusei). Such cases may require alternative antifungal therapy.

Susceptibility Testing Methods

Cryptococcus neoformans and filamentous fungi

No interpretive criteria have been established for Cryptococcus neoformans and filamentous fungi.

Candida species

Broth Dilution Techniques

Quantitative methods are used to determine antifungal minimum inhibitory concentrations (MICs). These MICs provide estimates of the susceptibility of Candida spp. to antifungal agents. MICs should be determined using a standardized procedure. Standardized procedures are based on a dilution method (broth)^1 with standardized inoculum concentrations of fluconazole powder. The MIC values should be interpreted according to the criteria provided in Table 1.

Diffusion Techniques

Qualitative methods that require measurement of zone diameters also provide reproducible estimates of the susceptibility of Candida spp. to an antifungal agent. One such standardized procedure^2 requires the use of standardized inoculum concentrations. This procedure uses paper disks impregnated with 25 µg of fluconazole to test the susceptibility of yeasts to fluconazole. Disk diffusion interpretive criteria are also provided in Table 1.

Table 1: Susceptibility Interpretive Criteria for Fluconazole against Candida species
 | Broth Dilution at 48 hours (MIC in µg/mL) |  |  | Disk Diffusion at 24 hours (Zone Diameters in mm)
Antifungal agent | Susceptible (S) | Intermediate (I) [The intermediate category is sometimes called Susceptible-Dose Dependent (SDD) and both categories are equivalent for fluconazole.] | Resistant (R) | Susceptible (S) | Intermediate (I) | Resistant (R)
Fluconazole [Isolates of C. krusei are assumed to be intrinsically resistant to fluconazole and their MICs and/or zone diameters should not be interpreted using this scale.] | ≤ 8.0 | 16–32 | ≥64 | ≥19 | 15–18 | ≤14

A report of Susceptible (S) indicates that the antimicrobial drug is likely to inhibit growth of the microorganism if the antimicrobial drug reaches the concentration usually achievable at the site of infection.

A report of Intermediate (I) indicates that an infection due to the isolate may be appropriately treated in body sites where the drugs are physiologically concentrated or when a high dosage of drug is used.

A report of Resistant (R) indicates that the antimicrobial is not likely to inhibit growth of the pathogen if the antimicrobial drug reaches the concentrations usually achievable at the infection site; other therapy should be selected.

Quality Control

Standardized susceptibility test procedures require the use of quality control organisms to control the technical aspects of the test procedures. Standardized fluconazole powder and 25 µg disks should provide the following range of values noted in Table 2. NOTE: Quality control microorganisms are specific strains of organisms with intrinsic biological properties relating to resistance mechanisms and their genetic expression within fungi; the specific strains used for microbiological control are not clinically significant.

Table 2: Acceptable Quality Control Ranges for Fluconazole to be Used in Validation of Susceptibility Test Results
QC Strain | Macrodilution (MIC in µg/mL) @ 48 hours | Microdilution (MIC in µg/mL) @ 48 hours | Disk Diffusion (Zone Diameter in mm) @ 24 hours
Candida parapsilosis ATCC 22019 | 2.0–8.0 | 1.0–4.0 | 22–33
Candida krusei ATCC 6258 | 16–64 | 16–128 | --- [Quality control ranges have not been established for this strain/antifungal agent combination due to their extensive interlaboratory variation during initial quality control studies.]
Candida albicans ATCC 90028 | --- | --- | 28–39
Candida tropicalis ATCC 750 | --- | --- | 26–37

INDICATIONS AND USAGE

Fluconazole is indicated for the treatment of:

1. Vaginal candidiasis (vaginal yeast infections due to Candida).
2. Oropharyngeal and esophageal candidiasis. In open noncomparative studies of relatively small numbers of patients, fluconazole was also effective for the treatment of Candida urinary tract infections, peritonitis, and systemic Candida infections including candidemia, disseminated candidiasis, and pneumonia.
3. Cryptococcal meningitis. Before prescribing fluconazole for AIDS patients with cryptococcal meningitis, please see CLINICAL STUDIES section. Studies comparing fluconazole to amphotericin B in non-HIV infected patients have not been conducted.

Prophylaxis

Fluconazole is also indicated to decrease the incidence of candidiasis in patients undergoing bone marrow transplantation who receive cytotoxic chemotherapy and/or radiation therapy.

Specimens for fungal culture and other relevant laboratory studies (serology, histopathology) should be obtained prior to therapy to isolate and identify causative organisms. Therapy may be instituted before the results of the cultures and other laboratory studies are known; however, once these results become available, anti-infective therapy should be adjusted accordingly.

CLINICAL STUDIES

Cryptococcal meningitis

In a multicenter study comparing fluconazole (200 mg/day) to amphotericin B (0.3 mg/kg/day) for treatment of cryptococcal meningitis in patients with AIDS, a multivariate analysis revealed three pretreatment factors that predicted death during the course of therapy: abnormal mental status, cerebrospinal fluid cryptococcal antigen titer greater than 1:1024, and cerebrospinal fluid white blood cell count of less than 20 cells/mm^3. Mortality among high risk patients was 33% and 40% for amphotericin B and fluconazole patients, respectively (p=0.58), with overall deaths 14% (9 of 63 subjects) and 18% (24 of 131 subjects) for the 2 arms of the study (p=0.48). Optimal doses and regimens for patients with acute cryptococcal meningitis and at high risk for treatment failure remain to be determined. (Saag, et al. N Engl J Med 1992; 326:83–9.)

Vaginal candidiasis

Two adequate and well-controlled studies were conducted in the U.S. using the 150 mg tablet. In both, the results of the fluconazole regimen were comparable to the control regimen (clotrimazole or miconazole intravaginally for 7 days) both clinically and statistically at the one month post-treatment evaluation.

The therapeutic cure rate, defined as a complete resolution of signs and symptoms of vaginal candidiasis (clinical cure), along with a negative KOH examination and negative culture for Candida (microbiologic eradication), was 55% in both the fluconazole group and the vaginal products group.

 | Fluconazole PO 150 mg tablet | Vaginal Product qhs × 7 days
Enrolled | 448 | 422
Evaluable at Late Follow-up | 347 (77%) | 327 (77%)
Clinical cure | 239/347 (69%) | 235/327 (72%)
Mycologic eradication | 213/347 (61%) | 196/327 (60%)
Therapeutic cure | 190/347 (55%) | 179/327 (55%)

Approximately three-fourths of the enrolled patients had acute vaginitis (<4 episodes/12 months) and achieved 80% clinical cure, 67% mycologic eradication, and 59% therapeutic cure when treated with a 150 mg fluconazole tablet administered orally. These rates were comparable to control products. The remaining one-fourth of enrolled patients had recurrent vaginitis (≥4 episodes/12 months) and achieved 57% clinical cure, 47% mycologic eradication, and 40% therapeutic cure. The numbers are too small to make meaningful clinical or statistical comparisons with vaginal products in the treatment of patients with recurrent vaginitis.

Substantially more gastrointestinal events were reported in the fluconazole group compared to the vaginal product group. Most of the events were mild to moderate. Because fluconazole was given as a single dose, no discontinuations occurred.

Parameter | Fluconazole PO | Vaginal Products
Evaluable patients | 448 | 422
With any adverse event | 141 (31%) | 112 (27%)
Nervous System | 90 (20%) | 69 (16%)
Gastrointestinal | 73 (16%) | 18 (4%)
With drug-related event | 117 (26%) | 67 (16%)
Nervous System | 61 (14%) | 29 (7%)
Headache | 58 (13%) | 28 (7%)
Gastrointestinal | 68 (15%) | 13 (3%)
Abdominal pain | 25 (6%) | 7 (2%)
Nausea | 30 (7%) | 3 (1%)
Diarrhea | 12 (3%) | 2 (<1%)
Application site event | 0 (0%) | 19 (5%)
Taste Perversion | 6 (1%) | 0 (0%)

Pediatric Studies

Oropharyngeal candidiasis

An open-label, comparative study of the efficacy and safety of fluconazole (2–3 mg/kg/day) and oral nystatin (400,000 I.U. 4 times daily) in immunocompromised children with oropharyngeal candidiasis was conducted. Clinical and mycological response rates were higher in the children treated with fluconazole.

Clinical cure at the end of treatment was reported for 86% of fluconazole treated patients compared to 46% of nystatin treated patients. Mycologically, 76% of fluconazole treated patients had the infecting organism eradicated compared to 11% for nystatin treated patients.

 | Fluconazole | Nystatin
Enrolled | 96 | 90
Clinical Cure | 76/88 (86%) | 36/78 (46%)
Mycological eradication [Subjects without follow-up cultures for any reason were considered nonevaluable for mycological response.] | 55/72 (76%) | 6/54 (11%)

The proportion of patients with clinical relapse 2 weeks after the end of treatment was 14% for subjects receiving fluconazole and 16% for subjects receiving nystatin. At 4 weeks after the end of treatment, the percentages of patients with clinical relapse were 22% for fluconazole and 23% for nystatin.

CONTRAINDICATIONS

Fluconazole is contraindicated in patients who have shown hypersensitivity to fluconazole or to any of its excipients. There is no information regarding cross-hypersensitivity between fluconazole and other azole antifungal agents. Caution should be used in prescribing fluconazole to patients with hypersensitivity to other azoles. Coadministration of terfenadine is contraindicated in patients receiving fluconazole at multiple doses of 400 mg or higher based upon results of a multiple dose interaction study. Coadministration of other drugs known to prolong the QT interval and which are metabolized via the enzyme CYP3A4 such as cisapride, astemizole, erythromycin, pimozide, and quinidine are contraindicated in patients receiving fluconazole. (See CLINICAL PHARMACOLOGY: Drug Interaction Studies and PRECAUTIONS.)

WARNINGS

(1) Hepatic injury

Fluconazole should be administered with caution to patients with liver dysfunction. Fluconazole has been associated with rare cases of serious hepatic toxicity, including fatalities primarily in patients with serious underlying medical conditions. In cases of fluconazole associated hepatotoxicity, no obvious relationship to total daily dose, duration of therapy, sex, or age of the patient has been observed. Fluconazole hepatotoxicity has usually, but not always, been reversible on discontinuation of therapy. Patients who develop abnormal liver function tests during fluconazole therapy should be monitored for the development of more severe hepatic injury. Fluconazole should be discontinued if clinical signs and symptoms consistent with liver disease develop that may be attributable to fluconazole.

(2) Anaphylaxis

In rare cases, anaphylaxis has been reported.

(3) Dermatologic

Exfoliative skin disorders during treatment with fluconazole have been reported. Fatal outcomes have been reported in patients with serious underlying diseases. Patients with deep seated fungal infections who develop rashes during treatment with fluconazole should be monitored closely and the drug discontinued if lesions progress. Fluconazole should be discontinued in patients treated for superficial fungal infection who develop a rash that may be attributed to fluconazole.

(4) Use in Pregnancy

There are no adequate and well-controlled studies of fluconazole in pregnant women. Available human data do not suggest an increased risk of congenital anomalies following a single maternal dose of 150 mg. A few published case reports describe a rare pattern of distinct congenital anomalies in infants exposed in utero to high dose maternal fluconazole (400–800 mg/day) during most or all of the first trimester. These reported anomalies are similar to those seen in animal studies. If this drug is used during pregnancy or if the patient becomes pregnant while taking the drug, the patient should be informed of the potential hazard to the fetus (See PRECAUTIONS, Pregnancy.)

PRECAUTIONS

General

Some azoles, including fluconazole, have been associated with prolongation of the QT interval on the electrocardiogram. During post-marketing surveillance, there have been rare cases of QT prolongation and torsade de pointes in patients taking fluconazole. Most of these reports involved seriously ill patients with multiple confounding risk factors, such as structural heart disease, electrolyte abnormalities, and concomitant medications that may have been contributory.

Fluconazole should be administered with caution to patients with these potentially proarrhythmic conditions.

Concomitant use of fluconazole and erythromycin has the potential to increase the risk of cardiotoxicity (prolonged QT interval, torsade de pointes) and consequently sudden heart death. This combination should be avoided.

Fluconazole should be administered with caution to patients with renal dysfunction.

Fluconazole is a potent CYP2C9 inhibitor and a moderate CYP3A4 inhibitor. Fluconazole treated patients who are concomitantly treated with drugs with a narrow therapeutic window metabolized through CYP2C9 and CYP3A4 should be monitored.

Fluconazole Powder for Oral Suspension contains sucrose and should not be used in patients with hereditary fructose, glucose/galactose malabsorption, and sucrase-isomaltase deficiency.

When driving vehicles or operating machines, it should be taken into account that occasionally dizziness or seizures may occur.

Single Dose

The convenience and efficacy of the single dose oral tablet of fluconazole regimen for the treatment of vaginal yeast infections should be weighed against the acceptability of a higher incidence of drug related adverse events with fluconazole (26%) versus intravaginal agents (16%) in U.S. comparative clinical studies. (See ADVERSE REACTIONS and CLINICAL STUDIES.)

Drug Interactions

(See CLINICAL PHARMACOLOGY: Drug Interaction Studies and CONTRAINDICATIONS.) Fluconazole is a potent inhibitor of cytochrome P450 (CYP) isoenzyme 2C9 and 2C19, and a moderate inhibitor of CYP3A4. In addition to the observed /documented interactions mentioned below, there is a risk of increased plasma concentration of other compounds metabolized by CYP2C9, CYP2C19 and CYP3A4 coadministered with fluconazole. Therefore, caution should be exercised when using these combinations and the patients should be carefully monitored. The enzyme inhibiting effect of fluconazole persists 4–5 days after discontinuation of fluconazole treatment due to the long half-life of fluconazole. Clinically or potentially significant drug interactions between fluconazole and the following agents/classes have been observed. These are described in greater detail below:

Oral hypoglycemics
Coumarin-type anticoagulants
Phenytoin
Cyclosporine
Rifampin
Theophylline
Terfenadine
Cisapride
Astemizole
Rifabutin
Voriconazole
Tacrolimus
Short-acting benzodiazepines
Tofacitinib
Triazolam
Oral Contraceptives
Pimozide
Quinidine
Hydrochlorothiazide
Alfentanil
Amitriptyline, nortriptyline
Amphotericin B
Azithromycin
Carbamazepine
Calcium Channel Blockers
Celecoxib
Cyclophosphamide
Fentanyl
Halofantrine
HMG-CoA reductase inhibitors
Losartan
Methadone
Non-steroidal anti-inflammatory drugs
Prednisone
Saquinavir
Sirolimus
Vinca Alkaloids
Vitamin A
Zidovudine

Oral hypoglycemics

Clinically significant hypoglycemia may be precipitated by the use of fluconazole with oral hypoglycemic agents; one fatality has been reported from hypoglycemia in association with combined fluconazole and glyburide use. Fluconazole reduces the metabolism of tolbutamide, glyburide, and glipizide and increases the plasma concentration of these agents. When fluconazole is used concomitantly with these or other sulfonylurea oral hypoglycemic agents, blood glucose concentrations should be carefully monitored and the dose of the sulfonylurea should be adjusted as necessary. (See CLINICAL PHARMACOLOGY: Drug Interaction Studies.)

Coumarin-type anticoagulants

Prothrombin time may be increased in patients receiving concomitant fluconazole and coumarin-type anticoagulants. In post-marketing experience, as with other azole antifungals, bleeding events (bruising, epistaxis, gastrointestinal bleeding, hematuria, and melena) have been reported in association with increases in prothrombin time in patients receiving fluconazole concurrently with warfarin. Careful monitoring of prothrombin time in patients receiving fluconazole and coumarin-type anticoagulants is recommended. Dose adjustment of warfarin may be necessary. (See CLINICAL PHARMACOLOGY: Drug Interaction Studies.)

Phenytoin

Fluconazole increases the plasma concentrations of phenytoin. Careful monitoring of phenytoin concentrations in patients receiving fluconazole and phenytoin is recommended. (See CLINICAL PHARMACOLOGY: Drug Interaction Studies.)

Cyclosporine

Fluconazole significantly increases cyclosporine levels in renal transplant patients with or without renal impairment. Careful monitoring of cyclosporine concentrations and serum creatinine is recommended in patients receiving fluconazole and cyclosporine. (See CLINICAL PHARMACOLOGY: Drug Interaction Studies). This combination may be used by reducing the dosage of cyclosporine depending on cyclosporine concentration.

Rifampin

Rifampin enhances the metabolism of concurrently administered fluconazole. Depending on clinical circumstances, consideration should be given to increasing the dose of fluconazole when it is administered with rifampin. (See CLINICAL PHARMACOLOGY: Drug Interaction Studies.)

Theophylline

Fluconazole increases the serum concentrations of theophylline. Careful monitoring of serum theophylline concentrations in patients receiving fluconazole and theophylline is recommended. (See CLINICAL PHARMACOLOGY: Drug Interaction Studies.)

Terfenadine

Because of the occurrence of serious cardiac dysrhythmias secondary to prolongation of the QTc interval in patients receiving azole antifungals in conjunction with terfenadine, interaction studies have been performed. One study at a 200 mg daily dose of fluconazole failed to demonstrate a prolongation in QTc interval. Another study at a 400 mg and 800 mg daily dose of fluconazole demonstrated that fluconazole taken in doses of 400 mg per day or greater significantly increases plasma levels of terfenadine when taken concomitantly. The combined use of fluconazole at doses of 400 mg or greater with terfenadine is contraindicated. (See CONTRAINDICATIONS and CLINICAL PHARMACOLOGY: Drug Interaction Studies.) The coadministration of fluconazole at doses lower than 400 mg/day with terfenadine should be carefully monitored.

Cisapride

There have been reports of cardiac events, including torsade de pointes, in patients to whom fluconazole and cisapride were coadministered. A controlled study found that concomitant fluconazole 200 mg once daily and cisapride 20 mg four times a day yielded a significant increase in cisapride plasma levels and prolongation of QTc interval. The combined use of fluconazole with cisapride is contraindicated. (See CONTRAINDICATIONS and CLINICAL PHARMACOLOGY: Drug Interaction Studies.)

Astemizole

Concomitant administration of fluconazole with astemizole may decrease the clearance of astemizole. Resulting increased plasma concentrations of astemizole can lead to QT prolongation and rare occurrences of torsade de pointes. Coadministration of fluconazole and astemizole is contraindicated.

Rifabutin

There have been reports that an interaction exists when fluconazole is administered concomitantly with rifabutin, leading to increased serum levels of rifabutin up to 80%. There have been reports of uveitis in patients to whom fluconazole and rifabutin were coadministered. Patients receiving rifabutin and fluconazole concomitantly should be carefully monitored. (See CLINICAL PHARMACOLOGY: Drug Interaction Studies.)

Voriconazole

Avoid concomitant administration of voriconazole and fluconazole. Monitoring for adverse events and toxicity related to voriconazole is recommended; especially, if voriconazole is started within 24 h after the last dose of fluconazole. (See CLINICAL PHARMACOLOGY: Drug Interaction Studies.)

Tacrolimus

Fluconazole may increase the serum concentrations of orally administered tacrolimus up to 5 times due to inhibition of tacrolimus metabolism through CYP3A4 in the intestines. No significant pharmacokinetic changes have been observed when tacrolimus is given intravenously. Increased tacrolimus levels have been associated with nephrotoxicity. Dosage of orally administered tacrolimus should be decreased depending on tacrolimus concentration. (See CLINICAL PHARMACOLOGY: Drug Interaction Studies.)

Short-acting Benzodiazepines

Following oral administration of midazolam, fluconazole resulted in substantial increases in midazolam concentrations and psychomotor effects. This effect on midazolam appears to be more pronounced following oral administration of fluconazole than with fluconazole administered intravenously. If short-acting benzodiazepines, which are metabolized by the cytochrome P450 system, are concomitantly administered with fluconazole, consideration should be given to decreasing the benzodiazepine dosage, and the patients should be appropriately monitored. (See CLINICAL PHARMACOLOGY: Drug Interaction Studies.)

Tofacitinib

Systemic exposure to tofacitinib is increased when tofacitinib is coadministered with fluconazole, a combined moderate CYP3A4 and potent CYP2C19 inhibitor. Reduce the dose of tofacitinib when given concomitantly with fluconazole (i.e., from 5 mg twice daily to 5 mg once daily as instructed in the XELJANZ® [tofacitinib] label). (See CLINICAL PHARMACOLOGY: Drug Interaction Studies.)

Triazolam

Fluconazole increases the AUC of triazolam (single dose) by approximately 50%, Cmax by 20–32%, and increases t½ by 25–50 % due to the inhibition of metabolism of triazolam. Dosage adjustments of triazolam may be necessary.

Oral Contraceptives

Two pharmacokinetic studies with a combined oral contraceptive have been performed using multiple doses of fluconazole. There were no relevant effects on hormone level in the 50 mg fluconazole study, while at 200 mg daily, the AUCs of ethinyl estradiol and levonorgestrel were increased 40% and 24%, respectively. Thus, multiple dose use of fluconazole at these doses is unlikely to have an effect on the efficacy of the combined oral contraceptive.

Pimozide

Although not studied in vitro or in vivo, concomitant administration of fluconazole with pimozide may result in inhibition of pimozide metabolism. Increased pimozide plasma concentrations can lead to QT prolongation and rare occurrences of torsade de pointes. Coadministration of fluconazole and pimozide is contraindicated.

Quinidine

Although not studied in vitro or in vivo, concomitant administration of fluconazole with quinidine may result in inhibition of quinidine metabolism. Use of quinidine has been associated with QT prolongation and rare occurrences of torsades de pointes. Coadministration of fluconazole and quinidine is contraindicated. (See CONTRAINDICATIONS.)

Hydrochlorothiazide

In a pharmacokinetic interaction study, coadministration of multiple dose hydrochlorothiazide to healthy volunteers receiving fluconazole increased plasma concentrations of fluconazole by 40%. An effect of this magnitude should not necessitate a change in the fluconazole dose regimen in subjects receiving concomitant diuretics.

Alfentanil

A study observed a reduction in clearance and distribution volume as well as prolongation of T½ of alfentanil following concomitant treatment with fluconazole. A possible mechanism of action is fluconazole's inhibition of CYP3A4. Dosage adjustment of alfentanil may be necessary.

Amitriptyline, nortriptyline

Fluconazole increases the effect of amitriptyline and nortriptyline. 5-nortriptyline and/or S-amitriptyline may be measured at initiation of the combination therapy and after one week. Dosage of amitriptyline/nortriptyline should be adjusted, if necessary.

Amphotericin B

Concurrent administration of fluconazole and amphotericin B in infected normal and immunosuppressed mice showed the following results: a small additive antifungal effect in systemic infection with C. albicans, no interaction in intracranial infection with Cryptococcus neoformans, and antagonism of the two drugs in systemic infection with A. fumigatus. The clinical significance of results obtained in these studies is unknown.

Azithromycin

An open-label, randomized, three-way crossover study in 18 healthy subjects assessed the effect of a single 1200 mg oral dose of azithromycin on the pharmacokinetics of a single 800 mg oral dose of fluconazole as well as the effects of fluconazole on the pharmacokinetics of azithromycin. There was no significant pharmacokinetic interaction between fluconazole and azithromycin.

Carbamazepine

Fluconazole inhibits the metabolism of carbamazepine and an increase in serum carbamazepine of 30% has been observed. There is a risk of developing carbamazepine toxicity. Dosage adjustment of carbamazepine may be necessary depending on concentration measurements/effect.

Calcium Channel Blockers

Certain calcium channel antagonists (nifedipine, isradipine, amlodipine, verapamil, and felodipine) are metabolized by CYP3A4. Fluconazole has the potential to increase the systemic exposure of the calcium channel antagonists. Frequent monitoring for adverse events is recommended.

Celecoxib

During concomitant treatment with fluconazole (200 mg daily) and celecoxib (200 mg), the celecoxib Cmax and AUC increased by 68% and 134%, respectively. Half of the celecoxib dose may be necessary when combined with fluconazole.

Cyclophosphamide

Combination therapy with cyclophosphamide and fluconazole results in an increase in serum bilirubin and serum creatinine. The combination may be used while taking increased consideration to the risk of increased serum bilirubin and serum creatinine.

Fentanyl

One fatal case of possible fentanyl fluconazole interaction was reported. The author judged that the patient died from fentanyl intoxication. Furthermore, in a randomized crossover study with 12 healthy volunteers it was shown that fluconazole delayed the elimination of fentanyl significantly. Elevated fentanyl concentration may lead to respiratory depression.

Halofantrine

Fluconazole can increase halofantrine plasma concentration due to an inhibitory effect on CYP3A4.

HMG-CoA reductase inhibitors

The risk of myopathy and rhabdomyolysis increases when fluconazole is coadministered with HMG-CoA reductase inhibitors metabolized through CYP3A4, such as atorvastatin and simvastatin, or through CYP2C9, such as fluvastatin. If concomitant therapy is necessary, the patient should be observed for symptoms of myopathy and rhabdomyolysis and creatinine kinase should be monitored. HMG-CoA reductase inhibitors should be discontinued if a marked increase in creatinine kinase is observed or myopathy/rhabdomyolysis is diagnosed or suspected.

Losartan

Fluconazole inhibits the metabolism of losartan to its active metabolite (E-31 74) which is responsible for most of the angiotensin II-receptor antagonism which occurs during treatment with losartan. Patients should have their blood pressure monitored continuously.

Methadone

Fluconazole may enhance the serum concentration of methadone. Dosage adjustment of methadone may be necessary.

Non-steroidal anti-inflammatory drugs

The Cmax and AUC of flurbiprofen were increased by 23% and 81%, respectively, when coadministered with fluconazole compared to administration of flurbiprofen alone. Similarly, the Cmax and AUC of the pharmacologically active isomer [S-(+)-ibuprofen] were increased by 15% and 82%, respectively, when fluconazole was coadministered with racemic ibuprofen (400 mg) compared to administration of racemic ibuprofen alone.

Although not specifically studied, fluconazole has the potential to increase the systemic exposure of other NSAIDs that are metabolized by CYP2C9 (e.g., naproxen, lornoxicam, meloxicam, diclofenac). Frequent monitoring for adverse events and toxicity related to NSAIDs is recommended. Adjustment of dosage of NSAIDs may be needed.

Prednisone

There was a case report that a liver-transplanted patient treated with prednisone developed acute adrenal cortex insufficiency when a three month therapy with fluconazole was discontinued. The discontinuation of fluconazole presumably caused an enhanced CYP3A4 activity which led to increased metabolism of prednisone. Patients on long-term treatment with fluconazole and prednisone should be carefully monitored for adrenal cortex insufficiency when fluconazole is discontinued.

Saquinavir

Fluconazole increases the AUC of saquinavir by approximately 50%, Cmax by approximately 55%, and decreases clearance of saquinavir by approximately 50% due to inhibition of saquinavir's hepatic metabolism by CYP3A4 and inhibition of P-glycoprotein. Dosage adjustment of saquinavir may be necessary.

Sirolimus

Fluconazole increases plasma concentrations of sirolimus presumably by inhibiting the metabolism of sirolimus via CYP3A4 and P-glycoprotein. This combination may be used with a dosage adjustment of sirolimus depending on the effect/concentration measurements.

Vinca Alkaloids

Although not studied, fluconazole may increase the plasma levels of the vinca alkaloids (e.g., vincristine and vinblastine) and lead to neurotoxicity, which is possibly due to an inhibitory effect on CYP3A4.

Vitamin A

Based on a case report in one patient receiving combination therapy with all-trans-retinoid acid (an acid form of vitamin A) and fluconazole, CNS related undesirable effects have developed in the form of pseudotumour cerebri, which disappeared after discontinuation of fluconazole treatment. This combination may be used but the incidence of CNS related undesirable effects should be borne in mind.

Zidovudine

Fluconazole increases Cmax and AUC of zidovudine by 84% and 74%, respectively, due to an approximately 45% decrease in oral zidovudine clearance. The half-life of zidovudine was likewise prolonged by approximately 128% following combination therapy with fluconazole. Patients receiving this combination should be monitored for the development of zidovudine-related adverse reactions. Dosage reduction of zidovudine may be considered.

Physicians should be aware that interaction studies with medications other than those listed in the CLINICAL PHARMACOLOGY section have not been conducted, but such interactions may occur.

Carcinogenesis, Mutagenesis, and Impairment of Fertility

Fluconazole showed no evidence of carcinogenic potential in mice and rats treated orally for 24 months at doses of 2.5, 5, or 10 mg/kg/day (approximately 2–7× the recommended human dose). Male rats treated with 5 and 10 mg/kg/day had an increased incidence of hepatocellular adenomas.

Fluconazole, with or without metabolic activation, was negative in tests for mutagenicity in 4 strains of S. typhimurium, and in the mouse lymphoma L5178Y system. Cytogenetic studies in vivo (murine bone marrow cells, following oral administration of fluconazole) and in vitro (human lymphocytes exposed to fluconazole at 1000 µg/mL) showed no evidence of chromosomal mutations.

Fluconazole did not affect the fertility of male or female rats treated orally with daily doses of 5, 10, or 20 mg/kg or with parenteral doses of 5, 25, or 75 mg/kg, although the onset of parturition was slightly delayed at 20 mg/kg PO. In an intravenous perinatal study in rats at 5, 20, and 40 mg/kg, dystocia and prolongation of parturition were observed in a few dams at 20 mg/kg (approximately 5–15× the recommended human dose) and 40 mg/kg, but not at 5 mg/kg. The disturbances in parturition were reflected by a slight increase in the number of stillborn pups and decrease of neonatal survival at these dose levels. The effects on parturition in rats are consistent with the species specific estrogen-lowering property produced by high doses of fluconazole. Such a hormone change has not been observed in women treated with fluconazole. (See CLINICAL PHARMACOLOGY.)

Pregnancy

Teratogenic Effects

Pregnancy Category C

Single 150 mg tablet use for Vaginal Candidiasis

There are no adequate and well-controlled studies of fluconazole in pregnant women. Available human data do not suggest an increased risk of congenital anomalies following a single maternal dose of 150 mg.

Pregnancy Category D

All other indications

A few published case reports describe a rare pattern of distinct congenital anomalies in infants exposed in utero to high dose maternal fluconazole (400–800 mg/day) during most or all of the first trimester. These reported anomalies are similar to those seen in animal studies. If this drug is used during pregnancy, or if the patient becomes pregnant while taking the drug, the patient should be informed of the potential hazard to the fetus. (See WARNINGS, Use in Pregnancy.)

Human Data

Several published epidemiologic studies do not suggest an increased risk of congenital anomalies associated with low dose exposure to fluconazole in pregnancy (most subjects received a single oral dose of 150 mg). A few published case reports describe a distinctive and rare pattern of birth defects among infants whose mothers received high-dose (400–800 mg/day) fluconazole during most or all of the first trimester of pregnancy. The features seen in these infants include: brachycephaly, abnormal facies, abnormal calvarial development, cleft palate, femoral bowing, thin ribs and long bones, arthrogryposis, and congenital heart disease. These effects are similar to those seen in animal studies.

Animal Data

Fluconazole was administered orally to pregnant rabbits during organogenesis in two studies at doses of 5, 10, and 20 mg/kg and at 5, 25, and 75 mg/kg, respectively. Maternal weight gain was impaired at all dose levels (approximately 0.25 to 4 times the 400 mg clinical dose based on BSA), and abortions occurred at 75 mg/kg (approximately 4 times the 400 mg clinical dose based on BSA); no adverse fetal effects were observed.

In several studies in which pregnant rats received fluconazole orally during organogenesis, maternal weight gain was impaired and placental weights were increased at 25 mg/kg. There were no fetal effects at 5 or 10 mg/kg; increases in fetal anatomical variants (supernumerary ribs, renal pelvis dilation) and delays in ossification were observed at 25 and 50 mg/kg and higher doses. At doses ranging from 80 to 320 mg/kg (approximately 2 to 8 times the 400 mg clinical dose based on BSA), embryolethality in rats was increased and fetal abnormalities included wavy ribs, cleft palate, and abnormal cranio-facial ossification. These effects are consistent with the inhibition of estrogen synthesis in rats and may be a result of known effects of lowered estrogen on pregnancy, organogenesis, and parturition.

Nursing Mothers

Fluconazole is secreted in human milk at concentrations similar to maternal plasma concentrations. Caution should be exercised when fluconazole is administered to a nursing woman.

Pediatric Use

An open-label, randomized, controlled trial has shown fluconazole to be effective in the treatment of oropharyngeal candidiasis in children 6 months to 13 years of age. (See CLINICAL STUDIES.)

The use of fluconazole in children with cryptococcal meningitis, Candida esophagitis, or systemic Candida infections is supported by the efficacy shown for these indications in adults and by the results from several small noncomparative pediatric clinical studies. In addition, pharmacokinetic studies in children (see CLINICAL PHARMACOLOGY) have established a dose proportionality between children and adults. (See DOSAGE AND ADMINISTRATION.)

In a noncomparative study of children with serious systemic fungal infections, most of which were candidemia, the effectiveness of fluconazole was similar to that reported for the treatment of candidemia in adults. Of 17 subjects with culture-confirmed candidemia, 11 of 14 (79%) with baseline symptoms (3 were asymptomatic) had a clinical cure; 13/15 (87%) of evaluable patients had a mycologic cure at the end of treatment but two of these patients relapsed at 10 and 18 days, respectively, following cessation of therapy.

The efficacy of fluconazole for the suppression of cryptococcal meningitis was successful in 4 of 5 children treated in a compassionate-use study of fluconazole for the treatment of life-threatening or serious mycosis. There is no information regarding the efficacy of fluconazole for primary treatment of cryptococcal meningitis in children.

The safety profile of fluconazole in children has been studied in 577 children ages 1 day to 17 years who received doses ranging from 1 to 15 mg/kg/day for 1 to 1,616 days. (See ADVERSE REACTIONS.)

Efficacy of fluconazole has not been established in infants less than 6 months of age. (See CLINICAL PHARMACOLOGY.) A small number of patients (29) ranging in age from 1 day to 6 months have been treated safely with fluconazole.

Geriatric Use

In non-AIDS patients, side effects possibly related to fluconazole treatment were reported in fewer patients aged 65 and older (9%, n =339) than for younger patients (14%, n=2240). However, there was no consistent difference between the older and younger patients with respect to individual side effects. Of the most frequently reported (>1%) side effects, rash, vomiting, and diarrhea occurred in greater proportions of older patients. Similar proportions of older patients (2.4%) and younger patients (1.5%) discontinued fluconazole therapy because of side effects. In post-marketing experience, spontaneous reports of anemia and acute renal failure were more frequent among patients 65 years of age or older than in those between 12 and 65 years of age. Because of the voluntary nature of the reports and the natural increase in the incidence of anemia and renal failure in the elderly, it is however not possible to establish a casual relationship to drug exposure.

Controlled clinical trials of fluconazole did not include sufficient numbers of patients aged 65 and older to evaluate whether they respond differently from younger patients in each indication. Other reported clinical experience has not identified differences in responses between the elderly and younger patients.

Fluconazole is primarily cleared by renal excretion as unchanged drug. Because elderly patients are more likely to have decreased renal function, care should be taken to adjust dose based on creatinine clearance. It may be useful to monitor renal function. (See CLINICAL PHARMACOLOGY and DOSAGE AND ADMINISTRATION.)

ADVERSE REACTIONS

Fluconazole is generally well tolerated.

In some patients, particularly those with serious underlying diseases such as AIDS and cancer, changes in renal and hematological function test results and hepatic abnormalities have been observed during treatment with fluconazole and comparative agents, but the clinical significance and relationship to treatment is uncertain.

In Patients Receiving a Single Dose for Vaginal Candidiasis

During comparative clinical studies conducted in the United States, 448 patients with vaginal candidiasis were treated with fluconazole, 150 mg single dose. The overall incidence of side effects possibly related to fluconazole was 26%. In 422 patients receiving active comparative agents, the incidence was 16%. The most common treatment-related adverse events reported in the patients who received 150 mg single dose fluconazole for vaginitis were headache (13%), nausea (7%), and abdominal pain (6%). Other side effects reported with an incidence equal to or greater than 1% included diarrhea (3%), dyspepsia (1%), dizziness (1%), and taste perversion (1%). Most of the reported side effects were mild to moderate in severity. Rarely, angioedema and anaphylactic reaction have been reported in marketing experience.

In Patients Receiving Multiple Doses for Other Infections

Sixteen percent of over 4000 patients treated with fluconazole in clinical trials of 7 days or more experienced adverse events. Treatment was discontinued in 1.5% of patients due to adverse clinical events and in 1.3% of patients due to laboratory test abnormalities.

Clinical adverse events were reported more frequently in HIV infected patients (21%) than in non-HIV infected patients (13%); however, the patterns in HIV infected and non-HIV infected patients were similar. The proportions of patients discontinuing therapy due to clinical adverse events were similar in the two groups (1.5%).

The following treatment-related clinical adverse events occurred at an incidence of 1% or greater in 4048 patients receiving fluconazole for 7 or more days in clinical trials: nausea 3.7%, headache 1.9%, skin rash 1.8%, vomiting 1.7%, abdominal pain 1.7%, and diarrhea 1.5%.

Hepatobiliary

In combined clinical trials and marketing experience, there have been rare cases of serious hepatic reactions during treatment with fluconazole. (See WARNINGS.) The spectrum of these hepatic reactions has ranged from mild transient elevations in transaminases to clinical hepatitis, cholestasis and fulminant hepatic failure, including fatalities. Instances of fatal hepatic reactions were noted to occur primarily in patients with serious underlying medical conditions (predominantly AIDS or malignancy) and often while taking multiple concomitant medications. Transient hepatic reactions, including hepatitis and jaundice, have occurred among patients with no other identifiable risk factors. In each of these cases, liver function returned to baseline on discontinuation of fluconazole.

In two comparative trials evaluating the efficacy of fluconazole for the suppression of relapse of cryptococcal meningitis, a statistically significant increase was observed in median AST (SGOT) levels from a baseline value of 30 IU/L to 41 IU/L in one trial and 34 IU/L to 66 IU/L in the other. The overall rate of serum transaminase elevations of more than 8 times the upper limit of normal was approximately 1% in fluconazole-treated patients in clinical trials. These elevations occurred in patients with severe underlying disease, predominantly AIDS or malignancies, most of whom were receiving multiple concomitant medications, including many known to be hepatotoxic. The incidence of abnormally elevated serum transaminases was greater in patients taking fluconazole concomitantly with one or more of the following medications: rifampin, phenytoin, isoniazid, valproic acid, or oral sulfonylurea hypoglycemic agents.

Post-Marketing Experience

In addition, the following adverse events have occurred during post-marketing experience.

Immunologic: In rare cases, anaphylaxis (including angioedema, face edema, and pruritus) has been reported.

Body as a Whole: Asthenia, fatigue, fever, malaise.

Cardiovascular: QT prolongation, torsade de pointes. (See PRECAUTIONS.)

Central Nervous System: Seizures, dizziness.

Hematopoietic and Lymphatic: Leukopenia, including neutropenia and agranulocytosis, thrombocytopenia.

Metabolic: Hypercholesterolemia, hypertriglyceridemia, hypokalemia.

Gastrointestinal: Cholestasis, dry mouth, hepatocellular damage, dyspepsia, vomiting.

Other Senses: Taste perversion.

Musculoskeletal System: myalgia.

Nervous System: Insomnia, paresthesia, somnolence, tremor, vertigo.

Skin and Appendages: Acute generalized exanthematous-pustulosis, drug eruption, increased sweating, exfoliative skin disorders including Stevens-Johnson syndrome and toxic epidermal necrolysis (see WARNINGS), alopecia.

Adverse Reactions in Children

The pattern and incidence of adverse events and laboratory abnormalities recorded during pediatric clinical trials are comparable to those seen in adults.

In Phase II/III clinical trials conducted in the United States and in Europe, 577 pediatric patients, ages 1 day to 17 years were treated with fluconazole at doses up to 15 mg/kg/day for up to 1,616 days. Thirteen percent of children experienced treatment-related adverse events. The most commonly reported events were vomiting (5%), abdominal pain (3%), nausea (2%), and diarrhea (2%). Treatment was discontinued in 2.3% of patients due to adverse clinical events and in 1.4% of patients due to laboratory test abnormalities. The majority of treatment-related laboratory abnormalities were elevations of transaminases or alkaline phosphatase.

Percentage of Patients With Treatment-Related Side Effects
 | Fluconazole | Comparative Agents
 | (N=577) | (N=451)
With any side effect | 13.0 | 9.3
Vomiting | 5.4 | 5.1
Abdominal pain | 2.8 | 1.6
Nausea | 2.3 | 1.6
Diarrhea | 2.1 | 2.2

OVERDOSAGE

There have been reports of overdose with fluconazole accompanied by hallucination and paranoid behavior.

In the event of overdose, symptomatic treatment (with supportive measures and gastric lavage if clinically indicated) should be instituted.

Fluconazole is largely excreted in urine. A three-hour hemodialysis session decreases plasma levels by approximately 50%.

In mice and rats receiving very high doses of fluconazole, clinical effects in both species included decreased motility and respiration, ptosis, lacrimation, salivation, urinary incontinence, loss of righting reflex, and cyanosis; death was sometimes preceded by clonic convulsions.

DOSAGE AND ADMINISTRATION

Dosage and Administration in Adults

Single Dose

Vaginal candidiasis

The recommended dosage of fluconazole for vaginal candidiasis is 150 mg as a single oral dose.

Multiple Dose

SINCE ORAL ABSORPTION IS RAPID AND ALMOST COMPLETE, THE DAILY DOSE OF FLUCONAZOLE IS THE SAME FOR ORAL (TABLETS AND SUSPENSION) AND INTRAVENOUS ADMINISTRATION. In general, a loading dose of twice the daily dose is recommended on the first day of therapy to result in plasma concentrations close to steady-state by the second day of therapy.

The daily dose of fluconazole for the treatment of infections other than vaginal candidiasis should be based on the infecting organism and the patient's response to therapy. Treatment should be continued until clinical parameters or laboratory tests indicate that active fungal infection has subsided. An inadequate period of treatment may lead to recurrence of active infection. Patients with AIDS and cryptococcal meningitis or recurrent oropharyngeal candidiasis usually require maintenance therapy to prevent relapse.

Oropharyngeal candidiasis

The recommended dosage of fluconazole for oropharyngeal candidiasis is 200 mg on the first day, followed by 100 mg once daily. Clinical evidence of oropharyngeal candidiasis generally resolves within several days, but treatment should be continued for at least 2 weeks to decrease the likelihood of relapse.

Esophageal candidiasis

The recommended dosage of fluconazole for esophageal candidiasis is 200 mg on the first day, followed by 100 mg once daily. Doses up to 400 mg/day may be used, based on medical judgment of the patient's response to therapy. Patients with esophageal candidiasis should be treated for a minimum of three weeks and for at least two weeks following resolution of symptoms.

Systemic Candida infections

For systemic Candida infections including candidemia, disseminated candidiasis, and pneumonia, optimal therapeutic dosage and duration of therapy have not been established. In open, noncomparative studies of small numbers of patients, doses of up to 400 mg daily have been used.

Urinary tract infections and peritonitis

For the treatment of Candida urinary tract infections and peritonitis, daily doses of 50–200 mg have been used in open, noncomparative studies of small numbers of patients.

Cryptococcal meningitis

The recommended dosage for treatment of acute cryptococcal meningitis is 400 mg on the first day, followed by 200 mg once daily. A dosage of 400 mg once daily may be used, based on medical judgment of the patient's response to therapy. The recommended duration of treatment for initial therapy of cryptococcal meningitis is 10–12 weeks after the cerebrospinal fluid becomes culture negative. The recommended dosage of fluconazole for suppression of relapse of cryptococcal meningitis in patients with AIDS is 200 mg once daily.

Prophylaxis in patients undergoing bone marrow transplantation

The recommended fluconazole daily dosage for the prevention of candidiasis in patients undergoing bone marrow transplantation is 400 mg, once daily. Patients who are anticipated to have severe granulocytopenia (less than 500 neutrophils per cu mm) should start fluconazole prophylaxis several days before the anticipated onset of neutropenia, and continue for 7 days after the neutrophil count rises above 1000 cells per cu mm.

Dosage and Administration in Children

The following dose equivalency scheme should generally provide equivalent exposure in pediatric and adult patients:

Pediatric Patients | Adults
3 mg/kg | 100 mg
6 mg/kg | 200 mg
12 [Some older children may have clearances similar to that of adults. Absolute doses exceeding 600 mg/day are not recommended.] mg/kg | 400 mg

Experience with fluconazole in neonates is limited to pharmacokinetic studies in premature newborns. (See CLINICAL PHARMACOLOGY.) Based on the prolonged half-life seen in premature newborns (gestational age 26 to 29 weeks), these children, in the first two weeks of life, should receive the same dosage (mg/kg) as in older children, but administered every 72 hours. After the first two weeks, these children should be dosed once daily. No information regarding fluconazole pharmacokinetics in full-term newborns is available.

Oropharyngeal candidiasis

The recommended dosage of fluconazole for oropharyngeal candidiasis in children is 6 mg/kg on the first day, followed by 3 mg/kg once daily. Treatment should be administered for at least 2 weeks to decrease the likelihood of relapse.

Esophageal candidiasis

For the treatment of esophageal candidiasis, the recommended dosage of fluconazole in children is 6 mg/kg on the first day, followed by 3 mg/kg once daily. Doses up to 12 mg/kg/day may be used, based on medical judgment of the patient's response to therapy. Patients with esophageal candidiasis should be treated for a minimum of three weeks and for at least 2 weeks following the resolution of symptoms.

Systemic Candida infections

For the treatment of candidemia and disseminated Candida infections, daily doses of 6–12 mg/kg/day have been used in an open, noncomparative study of a small number of children.

Cryptococcal meningitis

For the treatment of acute cryptococcal meningitis, the recommended dosage is 12 mg/kg on the first day, followed by 6 mg/kg once daily. A dosage of 12 mg/kg once daily may be used, based on medical judgment of the patient's response to therapy. The recommended duration of treatment for initial therapy of cryptococcal meningitis is 10–12 weeks after the cerebrospinal fluid becomes culture negative. For suppression of relapse of cryptococcal meningitis in children with AIDS, the recommended dose of fluconazole is 6 mg/kg once daily.

Dosage In Patients With Impaired Renal Function

Fluconazole is cleared primarily by renal excretion as unchanged drug. There is no need to adjust single dose therapy for vaginal candidiasis because of impaired renal function. In patients with impaired renal function who will receive multiple doses of fluconazole, an initial loading dose of 50 to 400 mg should be given. After the loading dose, the daily dose (according to indication) should be based on the following table:

Creatinine Clearance (mL/min) | Percent of Recommended Dose
>50 | 100%
≤50 (no dialysis) | 50%
Regular dialysis | 100% after each dialysis

Patients on regular dialysis should receive 100% of the recommended dose after each dialysis; on non-dialysis days, patients should receive a reduced dose according to their creatinine clearance.

These are suggested dose adjustments based on pharmacokinetics following administration of multiple doses. Further adjustment may be needed depending upon clinical condition.

When serum creatinine is the only measure of renal function available, the following formula (based on sex, weight, and age of the patient) should be used to estimate the creatinine clearance in adults:

Males: Weight (kg) × (140 – age)
72 × serum creatinine (mg/100 mL)

Females: 0.85 × above value

Although the pharmacokinetics of fluconazole has not been studied in children with renal insufficiency, dosage reduction in children with renal insufficiency should parallel that recommended for adults. The following formula may be used to estimate creatinine clearance in children:

K × linear length or height (cm)
serum creatinine (mg/100 mL)

(Where K=0.55 for children older than 1 year and 0.45 for infants.)

Administration

Fluconazole is administered orally. Fluconazole can be taken with or without food.

Directions for Mixing the Oral Suspension

Prepare a suspension at time of dispensing as follows: tap bottle until all the powder flows freely. To reconstitute, add 24 mL of distilled water or Purified Water (USP) to fluconazole bottle and shake vigorously to suspend powder. Each bottle will deliver 35 mL of suspension. The concentrations of the reconstituted suspensions are as follows:

Fluconazole Content per Bottle | Concentration of Reconstituted Suspension
350 mg | 10 mg/mL
1400 mg | 40 mg/mL

Note: Shake oral suspension well before using. Store reconstituted suspension between 86°F (30°C) and 41°F (5°C) and discard unused portion after 2 weeks. Protect from freezing.

HOW SUPPLIED

Fluconazole Tablets

Pink trapezoidal tablets containing 100 mg of fluconazole are packaged in bottles or unit dose blisters.

Fluconazole 100 mg Tablets: Embossed with "FLZ 100" on one side with no markings on the other side.

NDC 59762-5016-1 Bottles of 30

NDC 69189-5016-1 single dose pack with 1 tablet as repackaged by Avera McKennan Hospital

Storage: Store tablets below 86°F (30°C).

Fluconazole for Oral Suspension is supplied as an orange-flavored powder to provide 35 mL per bottle as follows:

NDC 59762-5029-1 Fluconazole 350 mg per bottle
NDC 59762-5030-1 Fluconazole 1400 mg per bottle

Storage: Store dry powder below 86°F (30°C). Store reconstituted suspension between 86°F (30°C) and 41°F (5°C) and discard unused portion after 2 weeks. Protect from freezing.

REFERENCES

1. Clinical and Laboratory Standards Institute (CLSI). Reference Method for Broth Dilution Antifungal Susceptibility Testing of Yeasts; Approved Standard-Third Edition. CLSI Document M27-A3, Clinical and Laboratory Standards Institute, 940 West Valley Road, Suite 1400, Wayne, PA, 19087, USA, 2008.
2. Clinical and Laboratory Standards Institute (CLSI). Methods for Antifungal Disk Diffusion Susceptibility Testing of Yeasts; Approved Guideline-Second Edition. CLSI Document M44-A2, Clinical and Laboratory Standards Institute, 940 West Valley Road, Suite 1400, Wayne, PA, 19087, USA, 2009.

LAB-0289-15.0
December 2014

PATIENT INFORMATION Fluconazole (fluconazole tablets)

This leaflet contains important information about FLUCONAZOLE (FLEW-kan-a-zol). It is not meant to take the place of your doctor's instructions. Read this information carefully before you take FLUCONAZOLE. Ask your doctor or pharmacist if you do not understand any of this information or if you want to know more about FLUCONAZOLE.

What Is FLUCONAZOLE?

FLUCONAZOLE is a tablet you swallow to treat vaginal yeast infections caused by a yeast called Candida. FLUCONAZOLE helps stop too much yeast from growing in the vagina so the yeast infection goes away.

FLUCONAZOLE is different from other treatments for vaginal yeast infections because it is a tablet taken by mouth. FLUCONAZOLE is also used for other conditions. However, this leaflet is only about using FLUCONAZOLE for vaginal yeast infections. For information about using FLUCONAZOLE for other reasons, ask your doctor or pharmacist. See the section of this leaflet for information about vaginal yeast infections.

What Is a Vaginal Yeast Infection?

It is normal for a certain amount of yeast to be found in the vagina. Sometimes too much yeast starts to grow in the vagina and this can cause a yeast infection. Vaginal yeast infections are common. About three out of every four adult women will have at least one vaginal yeast infection during their life.

Some medicines and medical conditions can increase your chance of getting a yeast infection. If you are pregnant, have diabetes, use birth control pills, or take antibiotics you may get yeast infections more often than other women. Personal hygiene and certain types of clothing may increase your chances of getting a yeast infection. Ask your doctor for tips on what you can do to help prevent vaginal yeast infections.

If you get a vaginal yeast infection, you may have any of the following symptoms:

- itching
- a burning feeling when you urinate
- redness
- soreness
- a thick white vaginal discharge that looks like cottage cheese

What To Tell Your Doctor Before You Start FLUCONAZOLE?

Do not take FLUCONAZOLE if you take certain medicines. They can cause serious problems. Therefore, tell your doctor about all the medicines you take including:

- diabetes medicines such as glyburide, tolbutamide, glipizide
- blood pressure medicines like hydrochlorothiazide, losartan, amlodipine, nifedipine or felodipine
- blood thinners such as warfarin
- cyclosporine, tacrolimus or sirolimus (used to prevent rejection of organ transplants)
- rifampin or rifabutin for tuberculosis
- astemizole for allergies
- phenytoin or carbamazepine to control seizures
- theophylline to control asthma
- cisapride for heartburn
- quinidine (used to correct disturbances in heart rhythm)
- amitriptyline or nortriptyline for depression
- pimozide for psychiatric illness
- amphotericin B or voriconazole for fungal infections
- erythromycin for bacterial infections
- cyclophosphamide or vinca alkaloids such as vincristine or vinblastine for treatment of cancer
- fentanyl, afentanil or methadone for chronic pain
- halofantrine for malaria
- lipid lowering drugs such as atorvastatin, simvastatin, and fluvastatin
- non-steroidal anti-inflammatory drugs including celecoxib, ibuprofen, and naproxen
- prednisone, a steroid used to treat skin, gastrointestinal, hematological or respiratory disorders
- antiviral medications used to treat HIV like saquinavir or zidovudine
- tofacitinib for rheumatoid arthritis
- vitamin A nutritional supplement

Since there are many brand names for these medicines, check with your doctor or pharmacist if you have any questions.

- are taking any over-the-counter medicines you can buy without a prescription, including natural or herbal remedies
- have any liver problems.
- have any other medical conditions
- are pregnant, plan to become pregnant, or think you might be pregnant. Your doctor will discuss whether FLUCONAZOLE is right for you.
- are breast-feeding. FLUCONAZOLE can pass through breast milk to the baby.
- are allergic to any other medicines including those used to treat yeast and other fungal infections.
- are allergic to any of the ingredients in FLUCONAZOLE. The main ingredient of FLUCONAZOLE is fluconazole. If you need to know the inactive ingredients, ask your doctor or pharmacist.

Who Should Not Take FLUCONAZOLE?

To avoid a possible serious reaction, do NOT take FLUCONAZOLE if you are taking erythromycin, astemizole, pimozide, quinidine, and cisapride (Propulsid®) since it can cause changes in heartbeat in some people if taken with FLUCONAZOLE.

How Should I Take FLUCONAZOLE?

Take FLUCONAZOLE by mouth with or without food. You can take FLUCONAZOLE at any time of the day.

FLUCONAZOLE keeps working for several days to treat the infection. Generally the symptoms start to go away after 24 hours. However, it may take several days for your symptoms to go away completely. If there is no change in your symptoms after a few days, call your doctor.

Just swallow 1 FLUCONAZOLE tablet to treat your vaginal yeast infection.

What Should I Avoid while Taking FLUCONAZOLE?

Some medicines can affect how well FLUCONAZOLE works. Check with your doctor before starting any new medicines within seven days of taking FLUCONAZOLE.

What Are the Possible Side Effects of FLUCONAZOLE?

Like all medicines, FLUCONAZOLE may cause some side effects that are usually mild to moderate.

The most common side effects of FLUCONAZOLE are:

- headache
- diarrhea
- nausea or upset stomach
- dizziness
- stomach pain
- changes in the way food tastes

Allergic reactions to FLUCONAZOLE are rare, but they can be very serious if not treated right away by a doctor. If you cannot reach your doctor, go to the nearest hospital emergency room. Signs of an allergic reaction can include shortness of breath; coughing; wheezing; fever; chills; throbbing of the heart or ears; swelling of the eyelids, face, mouth, neck, or any other part of the body; or skin rash, hives, blisters or skin peeling.

FLUCONAZOLE has been linked to rare cases of serious liver damage, including deaths, mostly in patients with serious medical problems. Call your doctor if your skin or eyes become yellow, your urine turns a darker color, your stools (bowel movements) are light-colored, or if you vomit or feel like vomiting or if you have severe skin itching.

In patients with serious conditions such as AIDS or cancer, rare cases of severe rashes with skin peeling have been reported. Tell your doctor right away if you get a rash while taking FLUCONAZOLE.

FLUCONAZOLE may cause other less common side effects besides those listed here. If you develop any side effects that concern you, call your doctor. For a list of all side effects, ask your doctor or pharmacist.

What to Do For an Overdose?

In case of an accidental overdose, call your doctor right away or go to the nearest emergency room.

How to Store FLUCONAZOLE?

Keep FLUCONAZOLE and all medicines out of the reach of children.

General Advice about Prescription Medicines

Medicines are sometimes prescribed for conditions that are mentioned in patient information leaflets. Do not use FLUCONAZOLE for a condition for which it was not prescribed. Do not give FLUCONAZOLE to other people, even if they have the same symptoms you have. It may harm them.

This leaflet summarizes the most important information about FLUCONAZOLE. If you would like more information, talk with your doctor. You can ask your pharmacist or doctor for information about FLUCONAZOLE that is written for health professionals.

This product's label may have been updated. For current full prescribing information, please visit www.greenstonellc.com

LAB-0367-9.0
December 2014